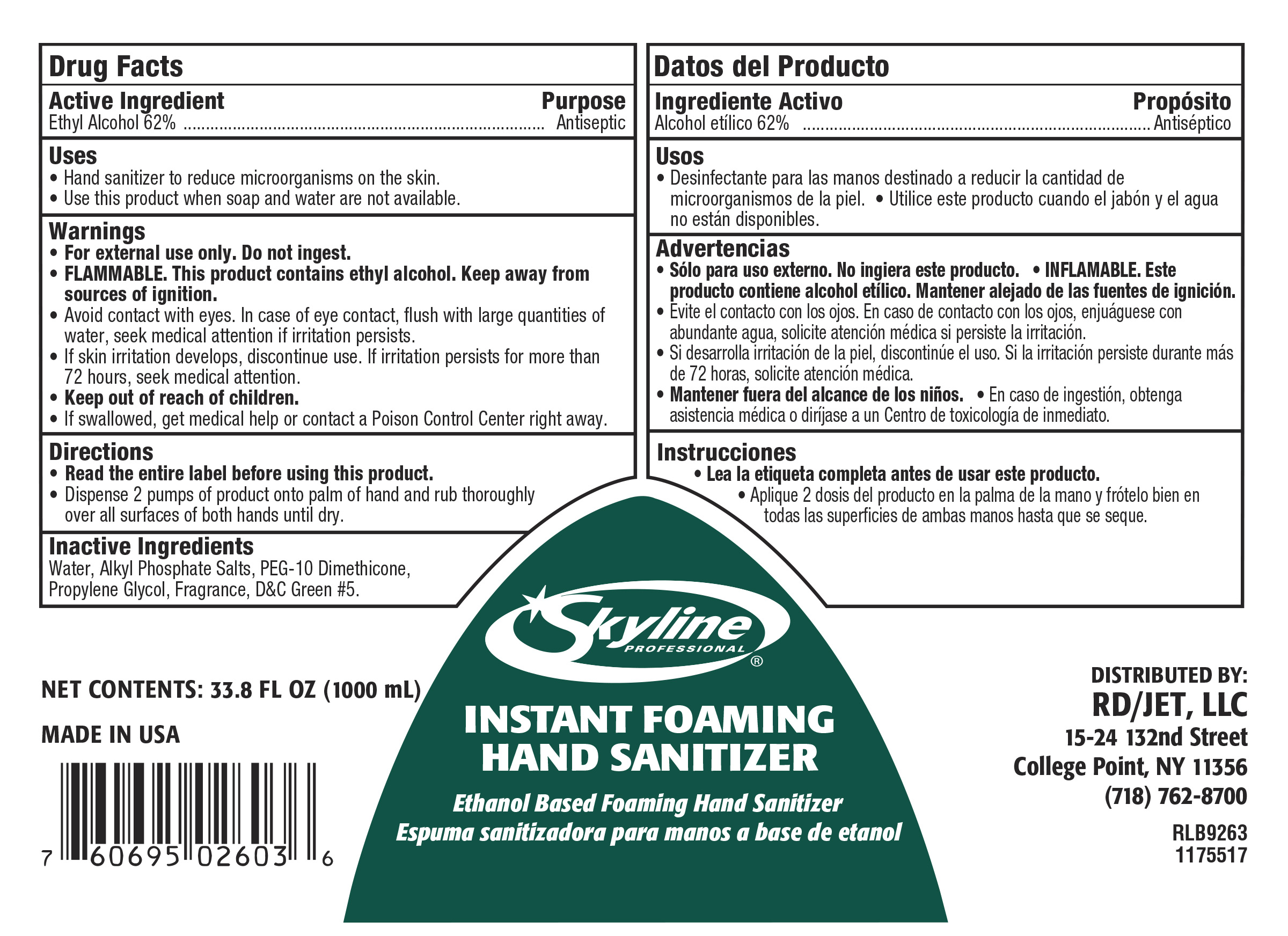 DRUG LABEL: Instant Foaming Hand Sanitizer
NDC: 56131-701 | Form: SOAP
Manufacturer: RD Food Service DBA Restaurant Depot
Category: otc | Type: HUMAN OTC DRUG LABEL
Date: 20190411

ACTIVE INGREDIENTS: ALCOHOL 0.62 mL/1 mL
INACTIVE INGREDIENTS: WATER; PROPYLENE GLYCOL; C20-22 ALKYL PHOSPHATE; D&C GREEN NO. 5; PEG-10 DIMETHICONE (600 CST)

Instant Foaming Hand Sanitizer

Active Ingredient

Ethyl Alcohol 62%

Uses

- Use hand sanitizer to reduce microorganisms on the skin.
- Use this product when soap and water are not available.

Warnings

- For external use only. Do not ingest.
- FLAMMABLE. This product contains ethyl alcohol. Keep away from sources of ignition.
- Avoid contact with eyes. In case of eye contact, flush with large quantities of water, seek medical attention if irritation persists.
- If skin irritation develops, discontinue use. If irritation persists for more than 72 hours, seek medical attention.
- Keep out of reach of children.
- If swallowed, get medical help or contact a Poison Control Center right away.

Directions

- Read the entire label before using this product.
- Dispense 2 pumps of product onto palm of hand and rub thoroughly over all surfaces of both hands until dry.

Inactive Ingredients

Water, Propylene Glycol, Acrylic Polymer, Alkyl Phosphate Salts, Fragrance, DC Green #5.

Purpose

Antiseptic

Alcohol Foaming Hand Sanitizer

KEEP OUT OF REACH OF CHILDREN

Alcohol Foaming Hand Sanitizer

RD_755